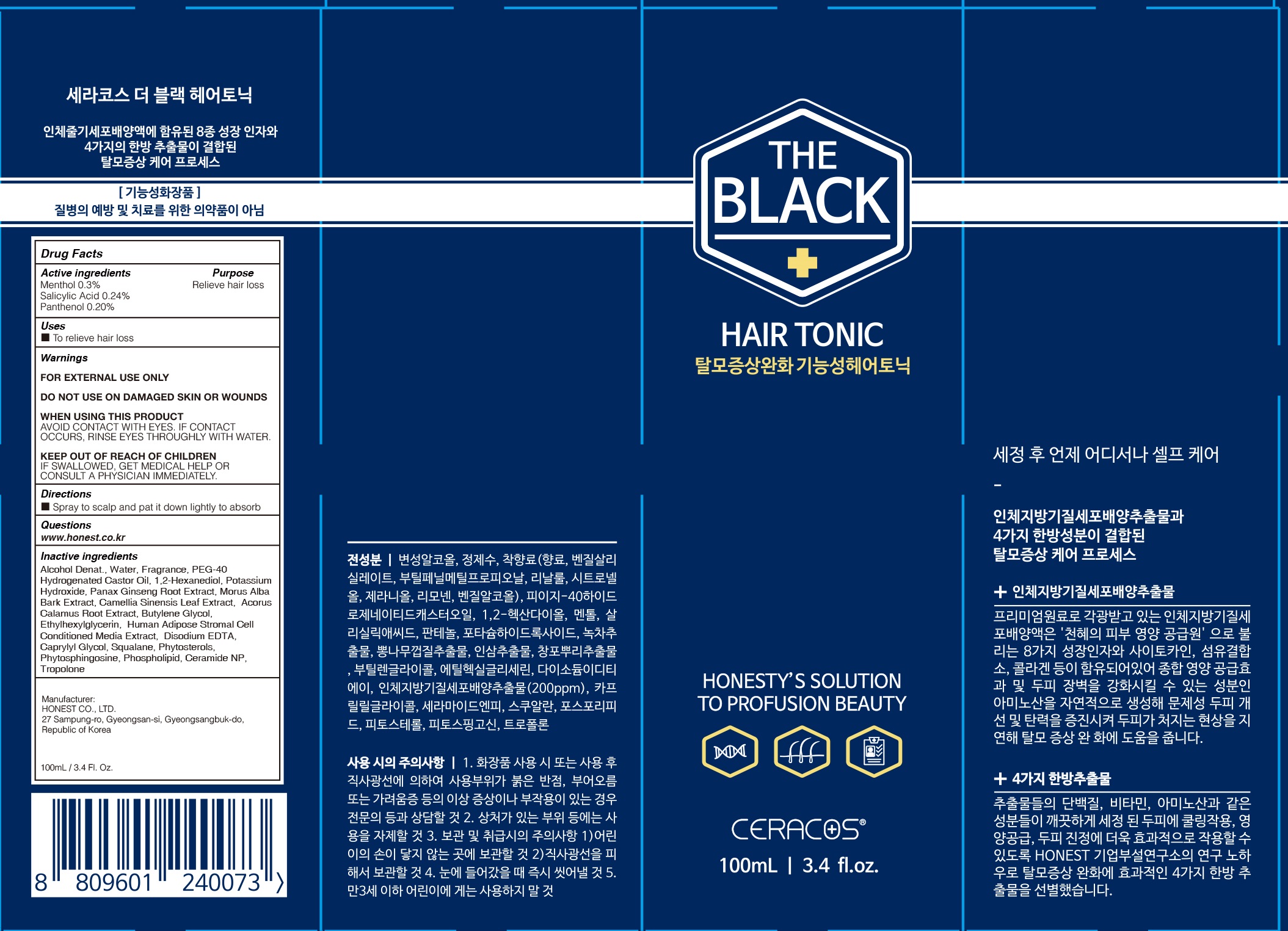 DRUG LABEL: CERACOS THE BLACK HAIR TONIC
NDC: 76904-020 | Form: SPRAY
Manufacturer: Honest Co., Ltd.
Category: otc | Type: HUMAN OTC DRUG LABEL
Date: 20200501

ACTIVE INGREDIENTS: Menthol 0.30 g/100 mL; Salicylic Acid 0.24 g/100 mL; Panthenol 0.20 g/100 mL
INACTIVE INGREDIENTS: Alcohol; Water; 1,2-Hexanediol; Caprylyl Glycol; Squalane; Phytosphingosine; Tropolone

ACTIVE INGREDIENT

Active ingredients: Menthol 0.3%, Salicylic Acid 0.24%, Panthenol 0.20%

INACTIVE INGREDIENT

Inactive ingredients:

Alcohol Denat., Water, Fragrance, PEG-40 Hydrogenated Castor Oil, 1,2-Hexanediol, Potassium Hydroxide, Panax Ginseng Root Extract, Morus Alba Bark Extract, Camellia Sinensis Leaf Extract, Acorus Calamus Root Extract, Butylene Glycol, Ethylhexylglycerin, Human Adipose Stromal Cell Conditioned Media Extract, Disodium EDTA, Caprylyl Glycol, Squalane, Phytosterols, Phytosphingosine, Phospholipid, Ceramide NP, Tropolone

PURPOSE

Purpose: Relieve hair loss

WARNINGS

FOR EXTERNAL USE ONLY

DO NOT USE ON DAMAGED SKIN OR WOUNDS

WHEN USING THIS PRODUCT
AVOID CONTACT WITH EYES. IF CONTACT OCCURS, RINSE EYES THROUGHLY WITH WATER.

KEEP OUT OF REACH OF CHILDREN

IF SWALLOWED, GET MEDICAL HELP OR CONSULT A PHYSICIAN IMMEDIATELY.

Uses

■ To relieve hair loss

Directions

■ Spray to scalp and pat it down lightly to absorb

QUESTIONS

■ www.honest.co.kr